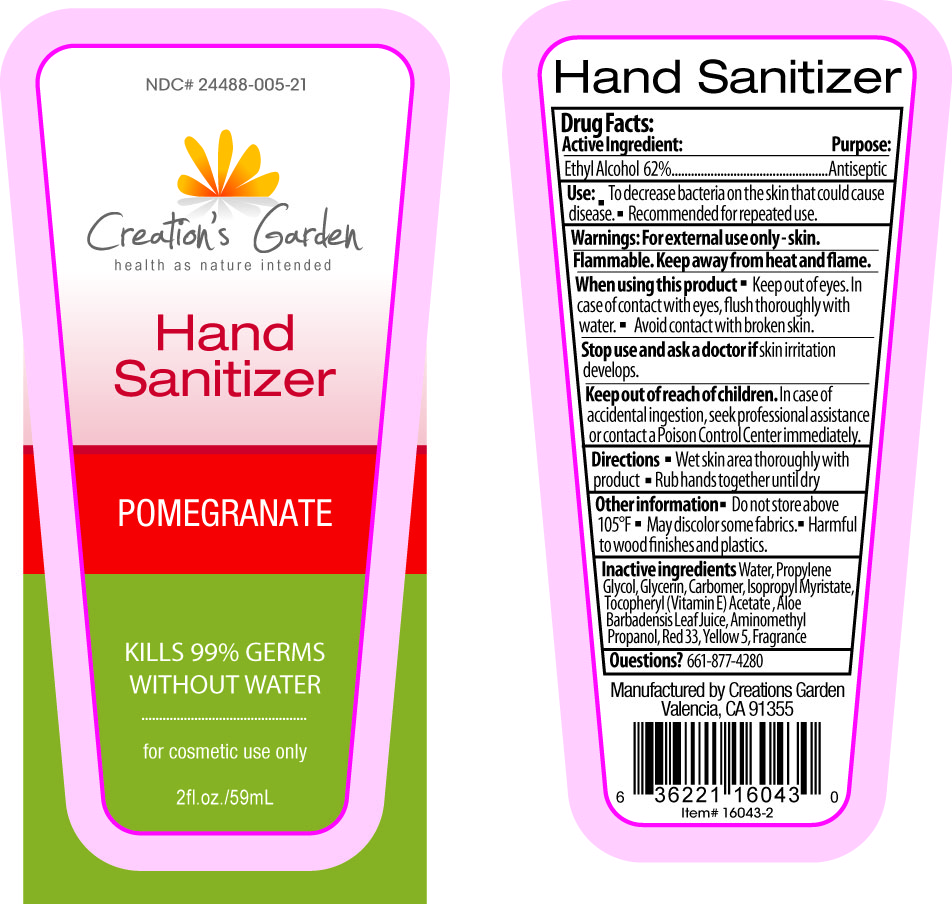 DRUG LABEL: Creations Garden
NDC: 24488-005 | Form: GEL
Manufacturer: Creations Garden Natural Products, Inc
Category: otc | Type: HUMAN OTC DRUG LABEL
Date: 20111025

ACTIVE INGREDIENTS: ALCOHOL 36.58 mL/59 mL
INACTIVE INGREDIENTS: Water; PROPYLENE GLYCOL; GLYCERIN; ISOPROPYL MYRISTATE; ALPHA-TOCOPHEROL ACETATE; ALOE VERA LEAF; AMINOMETHYLPROPANOL; FD&C YELLOW NO. 5; CARBOMER HOMOPOLYMER TYPE C; POMEGRANATE; D&C RED NO. 33

Drug Facts

ACTIVE INGREDIENT

Ethyl Alcohol 62%

Purpose

.................................Antiseptic

Use

- To decrease bacteria on the skin that could cause disease.
- Recommended for repeated use.

Warnings

For external use only. Flammable. Keep away from heat and flame.

When using this product

- Keep out of eyes. In case of contact with eyes, flush throughly with water
- Avoid contact with broken skin.

Stop use and ask a doctor

if skin irritation develops.

Keep out of reach of children.

In case of accidental ingestion, seek professional assistance or contact a Poison Control Center immediately.

Inactive Ingredients

Water, Propylene Glycol, Glycerin, Carbomer, Isopropyl Myristate, Tocopheryl (Vitamin E) Acetate, Aloe Barbadensis Leaf Juice, Aminomethyl Propanol, Red 33, Yellow 5, Fragrance

DOSAGE AND ADMINISTRATION

- Wet skin area thoroughly with product
- Rub hands together until dry.

Other information

- Do not store above 105°
- May discolor some fabrics.
- Harmful to wood finishes and plastics.

Question?

661-877-4280

PACKAGE LABEL

Placeholder Text